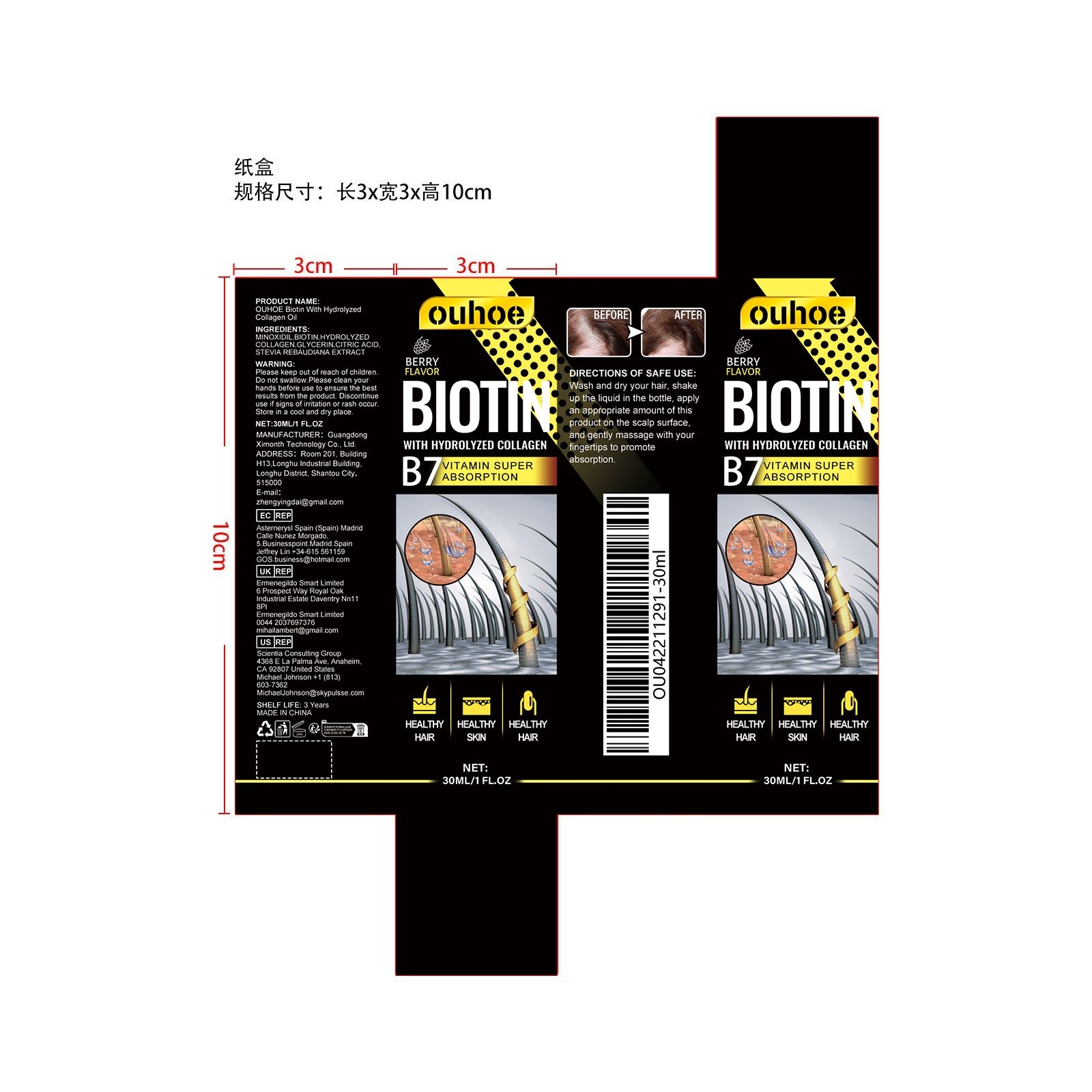 DRUG LABEL: Biotin With Hydrolyzed Collagen Oil
NDC: 84660-011 | Form: OIL
Manufacturer: Guangdong Ximonth Technology Co., Ltd.
Category: otc | Type: HUMAN OTC DRUG LABEL
Date: 20240909

ACTIVE INGREDIENTS: GLYCERIN 4.5 mg/30 mg; STEVIA REBAUDIANA WHOLE 3 mg/30 mg; HYDROLYZED PORCINE COLLAGEN (ENZYMATIC; 3000 MW) 4.5 mg/30 mg; BIOTIN 6 mg/30 mg
INACTIVE INGREDIENTS: MINOXIDIL 9 mg/30 mg; CITRIC ACID MONOHYDRATE 3 mg/30 mg

Active Ingredient(s)

BIOTIN、HYDROLYZED COLLAGEN、GLYCERIN、CITRIC ACID、STEVIA REBAUDIANA EXTRACT

Purpose

Make hair fuller

Use

Wash and dry your hair, shake up the liquid in the bottle, apply an appropriate amount of this product on the scalp surface, and gently massage with your fingertips to promote absorption.

Warnings

Please keep out of reach of children.Do not swallow.Please clean your hands before use to ensure the best results from the product.Discontinue use if signs of irritation or rash occur.Store in a cool and dry place.

Do not use

Discontinue use if signs of irritation or rash occur.

STOP USE

Discontinue use if signs of irritation or rash occur.

KEEP OUT OF REACH OF CHILDREN

Please keep out of reach of children. Do not swallow.

STORAGE AND HANDLING

Avoid freezing and excessive heat above 40C (104F) ）

Store in a cool and dry place.

INACTIVE INGREDIENT

MINOXIDIL